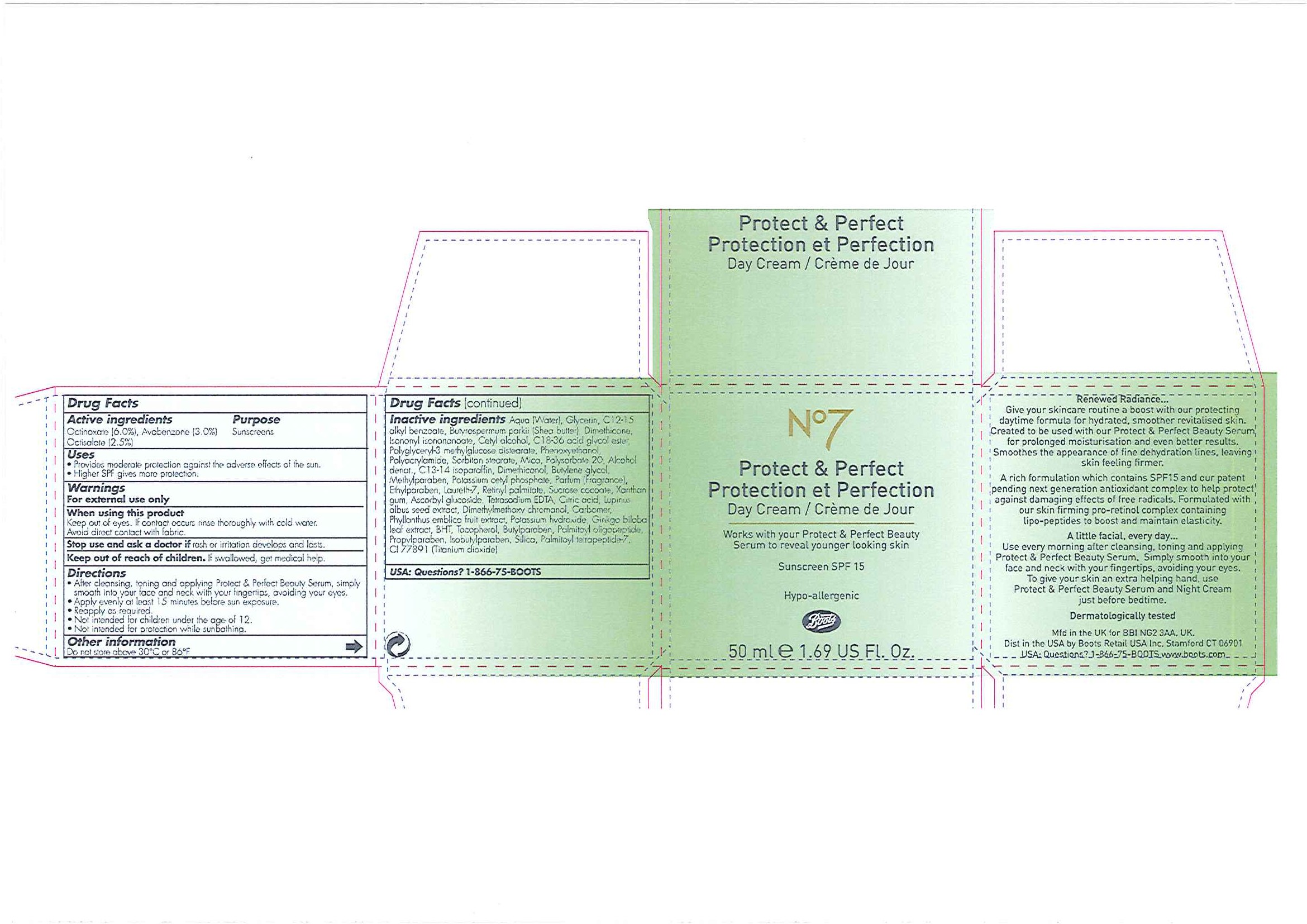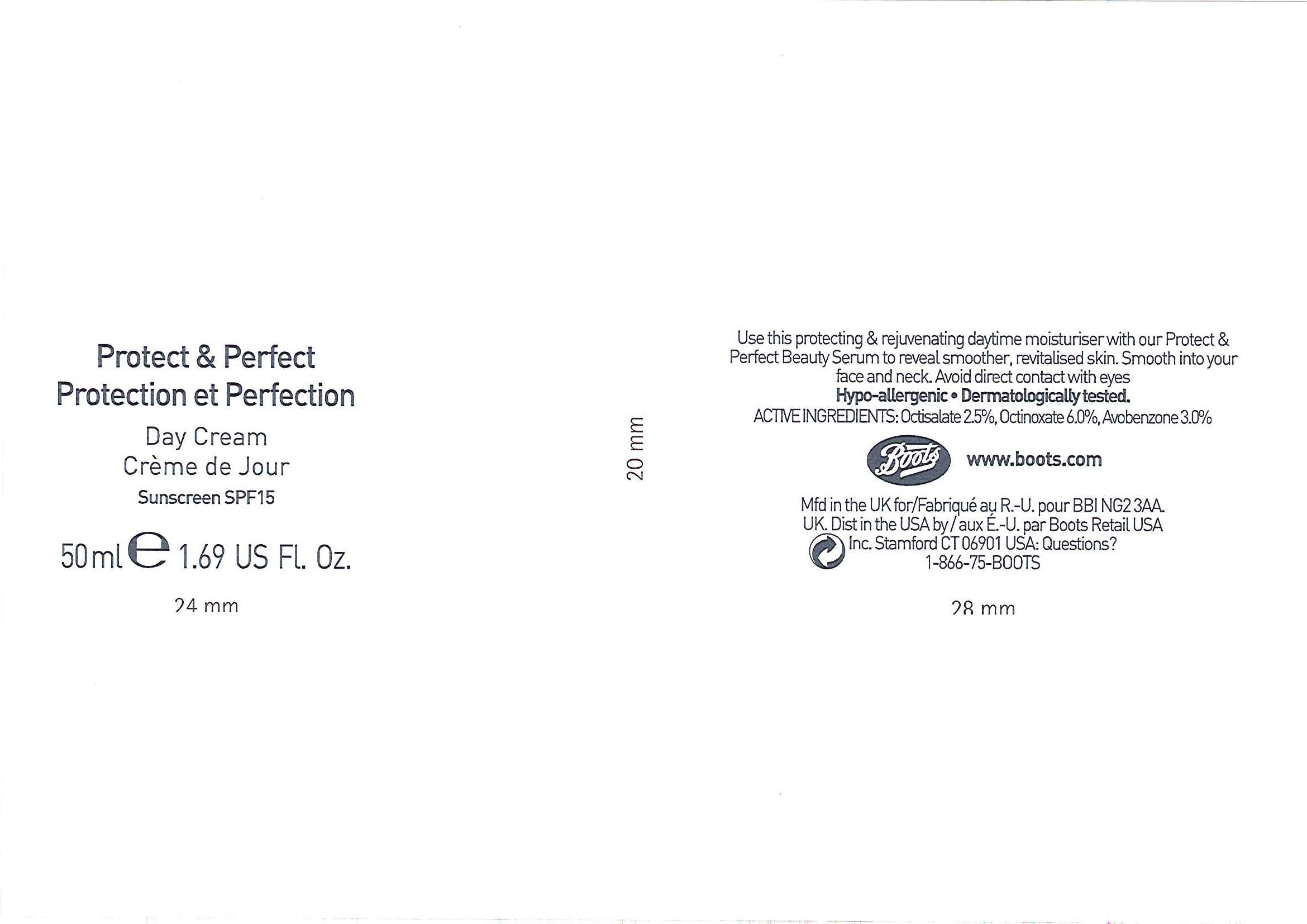 DRUG LABEL: No7 Protect and Perfect Day Sunscreen SPF 15
NDC: 11489-067 | Form: EMULSION
Manufacturer: BCM Ltd
Category: otc | Type: HUMAN OTC DRUG LABEL
Date: 20101206

ACTIVE INGREDIENTS: OCTINOXATE 3 mL/50 mL; AVOBENZONE 1.5 mL/50 mL; OCTISALATE 1.25 mL/50 mL
INACTIVE INGREDIENTS: WATER; GLYCERIN; SHEA BUTTER; DIMETHICONE; CETYL ALCOHOL; PHENOXYETHANOL; SORBITAN MONOSTEARATE; POLYSORBATE 20; BUTYLENE GLYCOL; METHYLPARABEN; ETHYLPARABEN; VITAMIN A PALMITATE; XANTHAN GUM; CITRIC ACID MONOHYDRATE; CARBOMER HOMOPOLYMER TYPE C; POTASSIUM HYDROXIDE; GINKGO; BUTYLATED HYDROXYTOLUENE; ALPHA-TOCOPHEROL; BUTYLPARABEN; PROPYLPARABEN; ISOBUTYLPARABEN; SILICON DIOXIDE; TITANIUM DIOXIDE

Carton and jar labelling

ACTIVE INGREDIENT

No7 Protect and Perfect Day Cream Sunscreen SPF 15

Active ingredients Purpose

Octinoxate (6.0%) Sunscreens

Avobenzone (3.0%)

Octisalate (2.5%)

Uses

- Provides moderate protection against the adverse effects of the sun
- Higher SPF gives more protection

Warnings

For external use only

When using this product

Keep out of eyes. If contact occurs rinse thoroughly with cold water

Avoid direct contact with fabric

Stop use and ask a doctor if rash or irritation develops and lasts.

KEEP OUT OF REACH OF CHILDREN

Keep our of reach of children. If swallowed, get medical help.

Directions

- After cleansing, toning and applying Protect and Perfect Beauty Serum, simply smooth into your face and neck with your fingertips, avoiding your eyes.
- Apply evenly at least 15 minutes before sun exposure.
- Reapply as required.
- Not intended for children under the age of 12.
- Not intended for protection while sunbathing.

Other information

Do not store above 30oC or 86oF

Inactive ingredients

Aqua (Water), Glycerin, C12-15 alkyl benzoate, Butyrospermum parkii (Shea butter), Dimethicone, Isononyl Isononanoate, Cetyl alcohol, C18-36 acid glycol ester, Polyglyceryl-3 methylglucose distearate, Phenoxyethanol, Polyacrylamide, Sorbitan stearate, Mica, Polysorbate 20, Alcohol denat., C13-14 isoparaffin, Dimethiconol, Butylene glycol, Methylparaben, Potassium cetyl phosphate, Parfum (Fragrance), Ethylparaben, Laureth-7, Retinyl palmitate, Sucrose cocoate, Xanthan gum, Ascorbyl glucoside, Tetrasodium EDTA, Citric acid, Lupinus albus seed extract, Dimethylmethoxy chromanol, Carbomer, Phyllanthus emblica fruit extract, Potassium hydroxide, Ginkgo biloba leaf extract, BHT, Tocopherol, Butylparaben, Palmitoyl oligopeptide, Propylparaben, Isobutylparaben, Silica, Palmitoyl tetrapeptide-7, CI 77891 (Titanium dioxide)

USA: Questions? 1-866-75-BOOTS

DESCRIPTION

Renewed Radiance ...

Give your skincare routine a boost with our protecting daytime formula for hydrated, smoother, revitalised skin. Created to be used with our Protect and Perfect Beauty Serum for prolonged moisturisation and even better results. Smoothes the appearance of fine dehydration lines, leaving skin feeling firmer.

A rich formulation which contains SPF15 and our patent pending next generation antioxidant complex to help protect against damaging effects of free radicals. Formulated with our skin firming pro-retinol complex containing lipo-peptides to boost and maintain elasticity.

A little facial, every day ...

Use every morning after cleansing, toning and applying Protect and Perfect Beauty Serum. Simply smooth into your face and neck with your fingertips, avoiding your eyes.

To give your skin an extra helping hand, use Protect and Perfect Beauty Serum and Night Cream just before bedtime.

Dermatologically tested

PATIENT COUNSELING INFORMATION

Mfd in the UK for BBI NG2 3AA. UK.

Dist in the USA by Boots Retail USA Inc. Stamford CT 06901

USA: Questions? 1-866-75-Boots

www.boots.com

DESCRIPTION

Use this protecting and rejuvenating daytime moisturiser with our Protect and Perfect Beauty Serum to reveal smoother, revitalised skin. Smooth into your face and neck.

Avoid direct contact with eyes.

Hypo-allergenic.

Dermatologically tested.

ACTIVE INGREDIENTS:

Octisalate 2.5%, Octinoxate 6.0%, Avobenzone 3.0%

PATIENT COUNSELING INFORMATION

Boots

www.boots.com

Mdf in the UK for/Fabriqué au R.-U. pour BBI NG2 3AA. UK

Dist in the USA by/aux É.U. par Boots Retail USA Inc. Stamford CT 06901

USA: Questions? 1-866-75-BOOTS

PACKAGE LABEL

No7

Protect and Perfect

Protection et Perfection

Day Cream / Créme de Jour

Works with your Protect and Perfect Beauty Serum to reveal younger looking skin

Sunscreen SPF 15

Hypo-allergenic

Boots

50ml e 1.69 US Fl. Oz

P and P Day Cream carton.jpg

PACKAGE LABEL

Protect and Perfect

Protection et Perfection

Day Cream

Créme de Jour

Sunscreen SPF15

50ml e 1.69 US Fl. Oz

P and P Day Cream carton.jpg